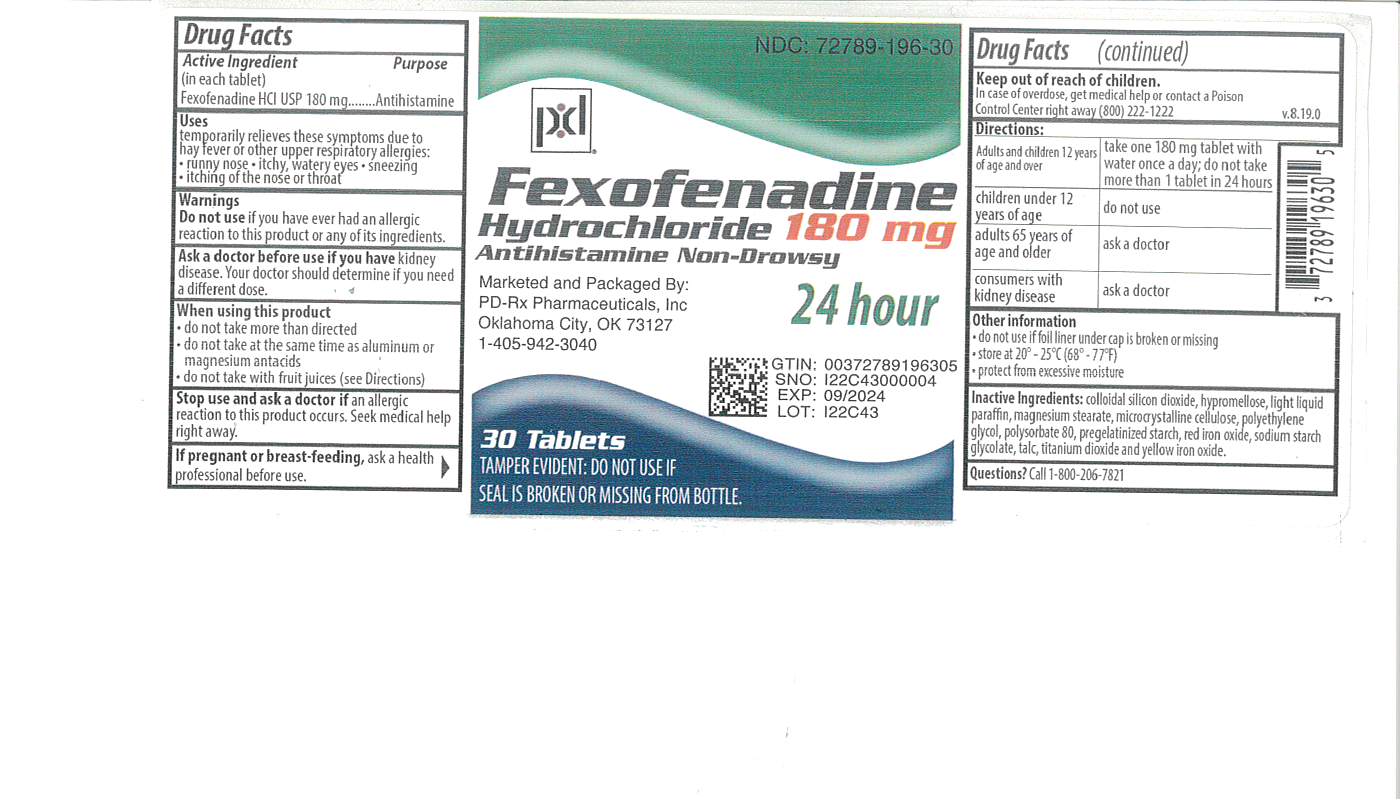 DRUG LABEL: Fexofenadine HCL
NDC: 72789-196 | Form: TABLET
Manufacturer: PD-Rx Pharmaceuticals, Inc.
Category: otc | Type: HUMAN OTC DRUG LABEL
Date: 20251008

ACTIVE INGREDIENTS: FEXOFENADINE HYDROCHLORIDE 180 mg/1 1
INACTIVE INGREDIENTS: LIGHT MINERAL OIL; MAGNESIUM STEARATE; CELLULOSE, MICROCRYSTALLINE; POLYETHYLENE GLYCOL 6000; POLYSORBATE 80; STARCH, CORN; FERRIC OXIDE RED; HYPROMELLOSE 2910 (6 MPA.S); FERRIC OXIDE YELLOW; SODIUM STARCH GLYCOLATE TYPE A POTATO; TALC; TITANIUM DIOXIDE; SILICON DIOXIDE

Fexofenadine Hydrochloride Tablets USP, 180 mg

ACTIVE INGREDIENT(S) in each tablet

Fexofenadine hydrochloride USP, 180 mg

PURPOSE

Antihistamine

USE(S)

temporarily relieves these symptoms due to hay fever or other upper respiratory allergies:

§ runny nose

§ sneezing

§ itchy, watery eyes

§ itching of the nose or throat

DO NOT USE

if you have ever had an allergic reaction to this product or any of its ingredients.

ASK A DOCTOR BEFORE USE IF

you have kidney disease. Your doctor should determine if you need a different dose.

WHEN USING THIS PRODUCT

§ do not take more than directed

§ do not take at the same time as aluminum or magnesium antacids

§ do not take with fruit juices (see Directions)

STOP USE AND ASK A DOCTOR IF

an allergic reaction to this product occurs. Seek medical help right away.
If pregnant or breast-feeding, ask a health professional before use.

KEEP OUT OF REACH OF CHILDREN

In case of overdose, get medical help or contact a Poison Control Center right away.

DIRECTIONS

adults and children 12 years of age and over | take one 180 mg tablet with water once a day; do not take more than 1 tablet in 24 hours
children under 12 years of age | do not use
adults 65 years of age and older | ask a doctor
consumers with kidney disease | ask a doctor

Other information

• Tamper-Evident: Do not use if seal is missing from bottle.
• store between 20° and 25°C (68° and 77°F)
• protect from excessive moisture

Inactive ingredients

Colloidal silicon dioxide, hypromellose, light liquid paraffin, magnesium stearate, microcrystalline cellulose, polyethylene glycol, polysorbate 80, pregelatinized starch, red iron oxide, sodium starch glycolate, talc, titanium dioxide and yellow iron oxide.

Questions?

Call 1-800-206-7821

HOW SUPPLIED

Fexofenadine HCL, 180 mg are pink, capsules debossed with 'J 44' and are supplied as follows:

NDC 72789-196-10 in bottles of 10 tablets

NDC 72789-196-30 in bottles of 30 tablets

NDC 72789-196-90 in bottles of 90 tablets

PRINCIPAL DISPLAY PANEL

Fexofenadine Hydrochloride Tablets USP, 180 mg